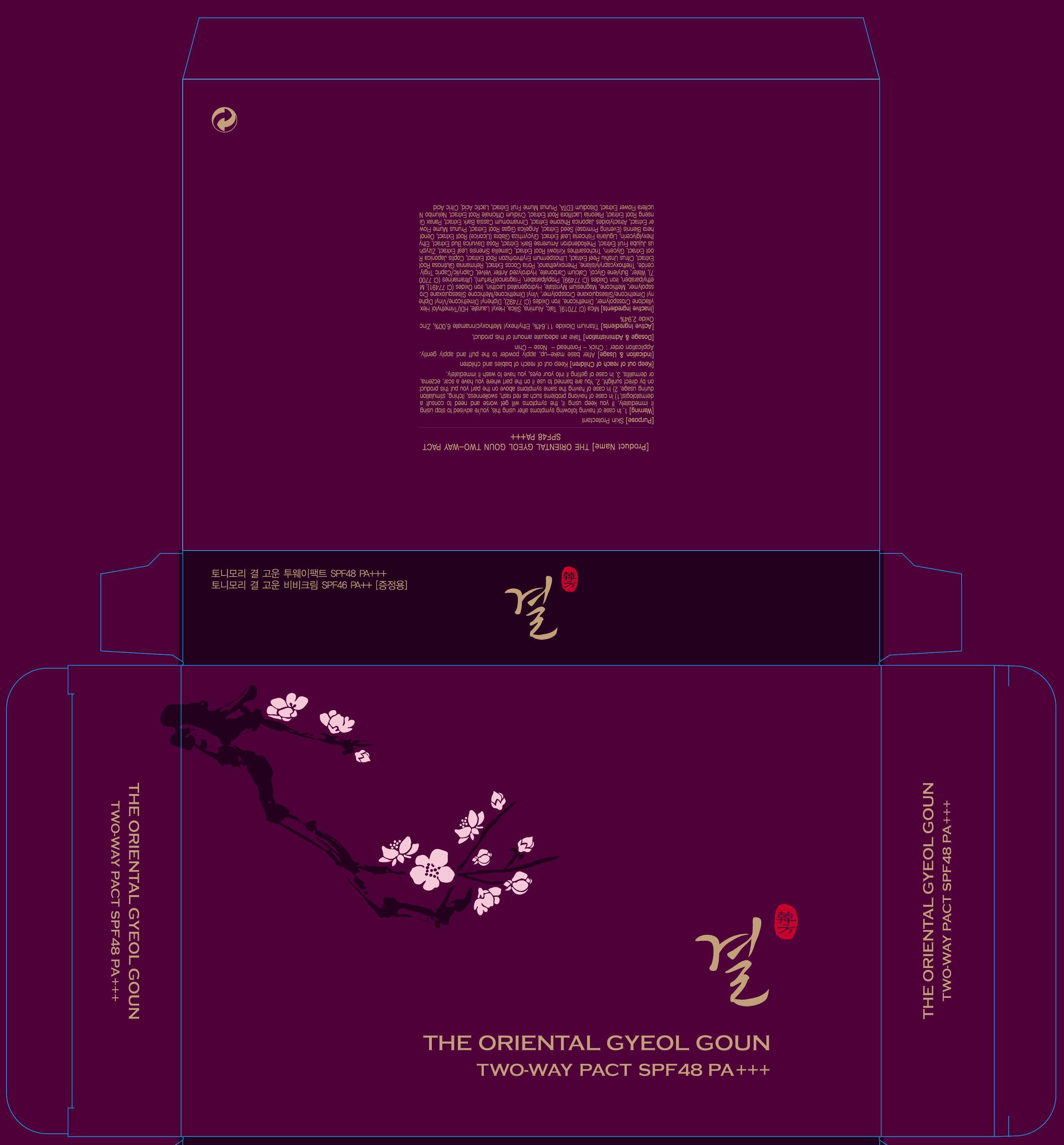 DRUG LABEL: The Oriental Gyeol Goun Two Way Pact
NDC: 59078-017 | Form: POWDER
Manufacturer: TONYMOLY CO., LTD.
Category: otc | Type: HUMAN OTC DRUG LABEL
Date: 20130803

ACTIVE INGREDIENTS: Titanium Dioxide 2.33 g/20 g; OCTINOXATE 1.2 g/20 g; Zinc Oxide 0.59 g/20 g
INACTIVE INGREDIENTS: Mica; Talc

ACTIVE INGREDIENT

Active Ingredients: Titanium Dioxide 11.64%, Ethylhexyl Methoxycinnamate 6.00%, Zinc Oxide 2.94%

INACTIVE INGREDIENT

Mica (CI 77019), Talc, Alumina, Silica, Hexyl Laurate, HDI/Trimethylol Hexyllactone Crosspolymer, Dimethicone, Iron Oxides (CI 77492), Diphenyl Dimethicone/Vinyl Diphenyl Dimethicone/Silsesquioxane Crosspolymer, Vinyl Dimethicone/Methicone Silsesquioxane Crosspolymer, Methicone, Magnesium Myristate, Hydrogenated Lecithin, Iron Oxides (CI 77491), Methylparaben, Iron Oxides (CI 77499), Propylparaben, Fragrance(Parfum), Ultramarines (CI 77007), Water, Butylene Glycol, Calcium Carbonate, Hydrolyzed Antler Velvet, Caprylic/Capric Triglyceride, Triethoxycaprylylsilane, Phenoxyethanol, Poria Cocos Extract, Rehmannia Glutinosa Root Extract, Citrus Unshiu Peel Extract, Lithospermum Erythrorhizon Root Extract, Coptis Japonica Root Extract, Glycerin, Trichosanthes Kirilowii Root Extract, Camellia Sinensis Leaf Extract, Zizyphus Jujuba Fruit Extract, Phellodendron Amurense Bark Extract, Rosa Davurica Bud Extract, Ethylhexylglycerin, Ligularia Fishceria Leaf Extract, Glycyrrhiza Glabra (Licorice) Root Extract, Oenothera Biennis (Evening Primrose) Seed Extract, Angelica Gigas Root Extract, Prunus Mume Flower Extract, Atractyloides Japonica Rhizome Extract, Cinnamomum Cassia Bark Extract, Panax Ginseng Root Extract, Paeonia Lactiflora Root Extract, Cnidium Officinale Root Extract, Nelumbo Nucifera Flower Extract, Disodium EDTA, Prunus Mume Fruit Extract, Lactic Acid, Citric Acid

PURPOSE

PURPOSE: SUNSCREEN

WARNINGS

1. In case of having following symptoms after using this, you're advised to stop using it immediately. If you keep using it, the symptoms will get worse and need to consult a dermatologist.
1) In case of having problems such as red rash, swollenness, itching, stimulation during usage.
2) In case of having the same symptoms above on the part you put this product on by direct sunlight.
2. You are banned to use it on the part where you have a scar, eczema, or dermatitis.
3. In case of getting it into your eyes, you have to wash it immediately.

KEEP OUT OF REACH OF CHILDREN

Keep out of reach of babies and children

INDICATIONS AND USAGE: After base make-up, apply powder to the puff and apply gently. Application order : Chick - Forehead - Nose - Chin

DOSAGE AND ADMINISTRATION: Take an adequate amount of this product.